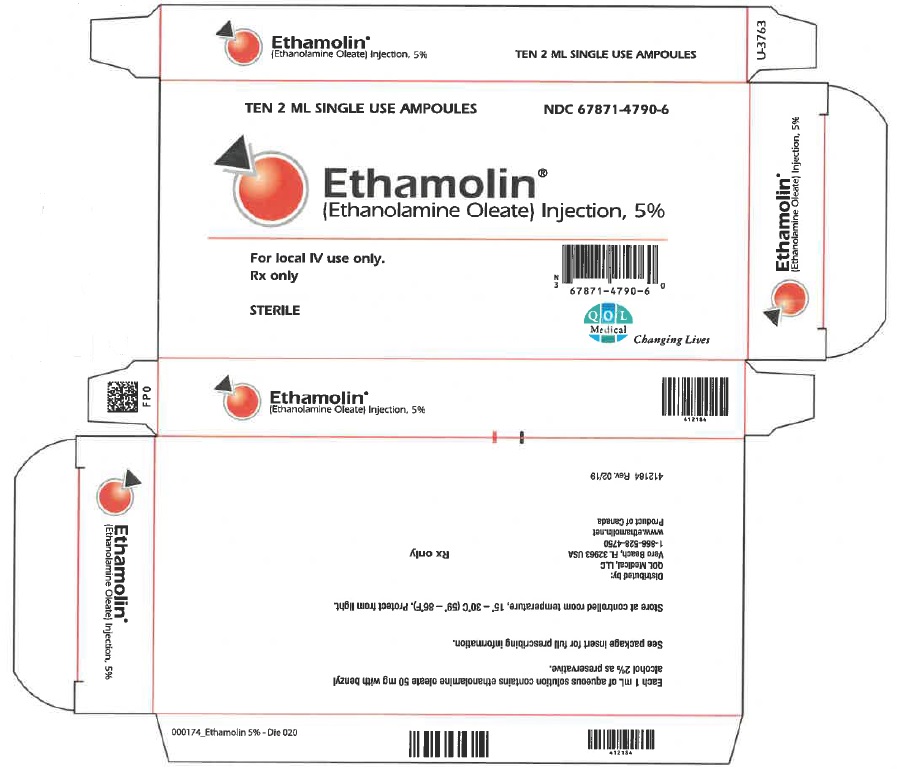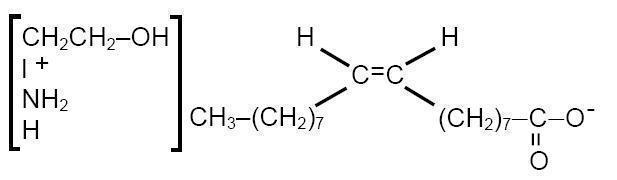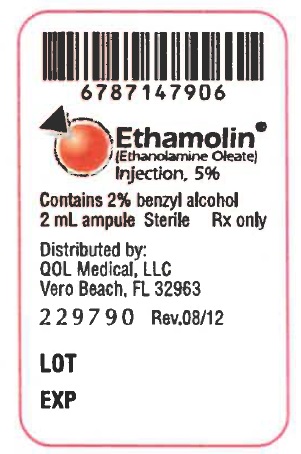 DRUG LABEL: Ethamolin
NDC: 67871-479 | Form: INJECTION, SOLUTION
Manufacturer: QOL Medical, LLC.
Category: prescription | Type: HUMAN PRESCRIPTION DRUG LABEL
Date: 20251210

ACTIVE INGREDIENTS: ETHANOLAMINE OLEATE 50 mg/1 mL
INACTIVE INGREDIENTS: BENZYL ALCOHOL; WATER

Ethamolin® (Ethanolamine Oleate) Injection, 5%. For Local Intravenous Use Only
Rx only

DESCRIPTION

ETHAMOLIN®(Ethanolamine Oleate) Injection is a mild sclerosing agent. Chemically it is C17H33COOH•NH2CH2CH2OH. It has the following structure:

The empirical formula is C20H41NO3, representing a molecular weight of 343.55.

ETHAMOLIN Injection consists of ethanolamine, a basic substance, which when combined with oleic acid, forms a clear pale-yellow to straw-colored, deliquescent oleate. The pH ranges from 8.2 to 9.2.

ETHAMOLIN Injection is a sterile, apyrogenic, aqueous solution containing in each mL approximately 50 mg of ethanolamine oleate with benzyl alcohol 2% by volume as preservative.

CLINICAL PHARMACOLOGY

When injected intravenously, ETHAMOLIN Injection acts primarily by irritation of the intimal endothelium of the vein and produces a sterile dose-related inflammatory response. This results in fibrosis and possible occlusion of the vein. ETHAMOLIN Injection also rapidly diffuses through the venous wall and produces a dose-related extravascular inflammatory reaction.

The oleic acid component of ETHAMOLIN Injection is responsible for the inflammatory response, and may also activate coagulation in vivoby release of tissue factor and activation of Hageman factor. The ethanolamine component, however, may inhibit fibrin clot formation by chelating calcium, so that a procoagulant action of ETHAMOLIN has not been demonstrated.

After injection, ETHAMOLIN disappears from the injection site within five minutes via the portal vein. When volumes larger than 20 mL are injected, some ETHAMOLIN also flows into the azygos vein through the periesophageal vein. In human autopsy studies it was found that within four days after injection there is neutrophil infiltration of the esophageal wall and hemorrhage within six days. Granulation tissue is first seen at ten days, red thrombi obliterating the varices by twenty days, and sclerosis of the varices by two and a half months. The time course of these findings suggests that sclerosis of esophageal varices will be a delayed rather than an immediate effect of the drug.

The minimum lethal dose of ETHAMOLIN Injection administered intravenously to rabbits is 130 mg/kg.

In dogs, ETHAMOLIN injected into the right atrium at a dose of 1 mL/kg over one minute has been shown to increase extravascular lung water. The maximum recommended human dose is 20 mL, or 0.4 mL/kg for a 50-kg person. The concentration of ETHAMOLIN reaching the lung in human treatment will be less than in the dog studies, but pleural effusions, pulmonary edema, pulmonary infiltration and pneumonitis have been reported in clinical trials, and minimizing the total per-session dose, especially in patients with concomitant cardiopulmonary disease, is recommended (see PRECAUTIONS).

INDICATIONS AND USAGE

ETHAMOLIN Injection is indicated for the treatment of patients with esophageal varices that have recently bled, to prevent rebleeding.

ETHAMOLIN is not indicated for the treatment of patients with esophageal varices that have not bled. There is no evidence that treatment of this population decreases the likelihood of bleeding.

Sclerotherapy with ETHAMOLIN has no beneficial effect upon portal hypertension, the cause of esophageal varices, so that recanalization and collateralization may occur, necessitating reinjection.

CONTRAINDICATIONS

ETHAMOLIN Injection should not be administered to subjects with a known hypersensitivity to ethanolamine, oleic acid, or ethanolamine oleate.

WARNINGS

ETHAMOLlN Injection should be used in pregnant women only when clearly needed (see PRECAUTIONS).

The practice of injecting varicosities of the leg with ETHAMOLlN Injection is not supported by adequately controlled clinical trials. Therefore, such use is not recommended.

PRECAUTIONS

Fatal anaphylactic shock was reported following injection of a larger than normal volume of ETHAMOLlN Injection into a male who had a known allergic disposition. Although there are only three known reports of anaphylaxis, the possibility of an anaphylactic reaction should be kept in mind, and the physician should be prepared to treat it appropriately. In extreme emergencies, 0.25 mL of a 1:1,000 intravenous solution of epinephrine (0.25 mg) should be used, and allergic reactions should be controlled with antihistamines.

Acute renal failure with spontaneous recovery followed injection of 15 to 20 mL of ETHAMOLIN Injection into two women.

The physician should bear in mind that severe injection necrosis may result from direct injection of sclerosing agents, especially if excessive volumes are used. At least one fatal case of extensive esophageal necrosis and death has been reported. The drug should be administered by physicians who are familiar with an acceptable injection technique.

Patients in Child Class C are more likely to develop esophageal ulceration than those in Classes A and B. Complications of ulceration, necrosis, and delayed esophageal perforation appear to occur more frequently when ETHAMOLIN Injection is injected submucosally. This route is not recommended.

In patients with concomitant cardiorespiratory disease, careful monitoring and minimization of the total dose per session is recommended.

Fatal aspiration pneumonia has occurred in elderly patients undergoing esophageal variceal sclerotherapy with ETHAMOLIN Injection. This adverse event appears to be procedure-related, rather than drug-related; but as aspiration of blood and/or stomach contents is not uncommon in patients with bleeding esophageal varices, special precautions should be taken to prevent its occurrence, especially in elderly and critically-ill subjects.

Pregnancy: (Teratogenic Effects: Pregnancy Category C)

Animal reproduction studies have not been conducted with ETHAMOLlN Injection. It is also not known whether ETHAMOLIN Injection can cause fetal harm when administered to a pregnant woman or can affect reproduction capacity. ETHAMOLIN Injection should be given to a pregnant woman only if clearly needed.

Nursing Mothers

It is not known whether this drug is excreted in human milk. Because many drugs are excreted in human milk, caution should be exercised when ETHAMOLlN Injection is administered to a nursing woman.

Pediatric Use

Safety and effectiveness in pediatric patients have not been established

ADVERSE REACTIONS

The reported frequency of complications/adverse events per injection session was 13%. The most common complications were pleural effusion/infiltration (2.1%), esophageal ulcer (2.1 %), pyrexia (1.8%), retrosternal pain (1.6%), esophageal stricture (1.3%), and pneumonia (1.2%).

Other adverse local esophageal reactions have also been reported at rates of 0.1 to 0.4%, including esophagitis, tearing of the esophagus, sloughing of the mucosa overlying the injected varix, ulceration, stricture, necrosis, periesophageal abscess and perforation (see PRECAUTIONS). These complications appear to be dependent upon the dose and the patient's clinical state.

Bacteremia has been observed in patients following injection of esophageal varices with ETHAMOLlN. Pyrexia and retrosternal pain are not infrequently observed during the post-injection period. Fatal aspiration pneumonia has occurred in patients with esophageal varices who underwent ETHAMOLIN Injection Sclerotherapy (see PRECAUTIONS). Anaphylactic shock and acute renal failure with spontaneous recovery have occurred (see PRECAUTIONS). A case of disseminated intravascular coagulation has been reported.

Spinal cord paralysis due to occlusion of the anterior spinal artery has been reported in one child eight hours after ETHAMOLIN sclerotherapy.

DRUG ABUSE AND DEPENDENCE

There is no potential for drug abuse or drug dependence.

OVERDOSAGE

Overdosage of ETHAMOLIN Injection can result in severe intramural necrosis of the esophagus. Complications resulting from such overdosage have resulted in death.

DOSAGE AND ADMINISTRATION

Local ETHAMOLIN Injection sclerotherapy of esophageal varices should be performed by physicians who are famillar with an acceptable technique. The usual intravenous dose is 1.5 to 5.0 mL per varix. The maximum dose per treatment session should not exceed 20 mL. Patients with significant liver dysfunction (Child Class C) or concomitant cardiopulmonary disease should usually receive less than the recommended maximum dose. Submucosal injections are not recommended as they reportedly are more likely to result in ulceration at the site of injection.

To obliterate the varix, injections may be made at the time of the acute bleeding episode and then after one week, six weeks, three months, and six months, as indicated.

Note: Parenteral drug products should be inspected visually for particulate matter and discoloration before administration whenever solution and container permit.

HOW SUPPLIED

NDC | SIZE
67871-4790-6 | 2 mL ampule

ETHAMOLIN® (Ethanolamine Oleate) Injection, 5% is available in 2 mL, sterile, single-use glass ampules supplied as boxes of 10 ampules.

Storage

Store at controlled room temperature, 15°- 30°C (59°- 86°F). Protect from light.

Distributed by:

QOL Medical, LLC

Vero Beach, FL 32963

www.ethamolin.net

phone 1-866-528-4750

fax 1-866-528-4749

412321 / Rev. 07/19